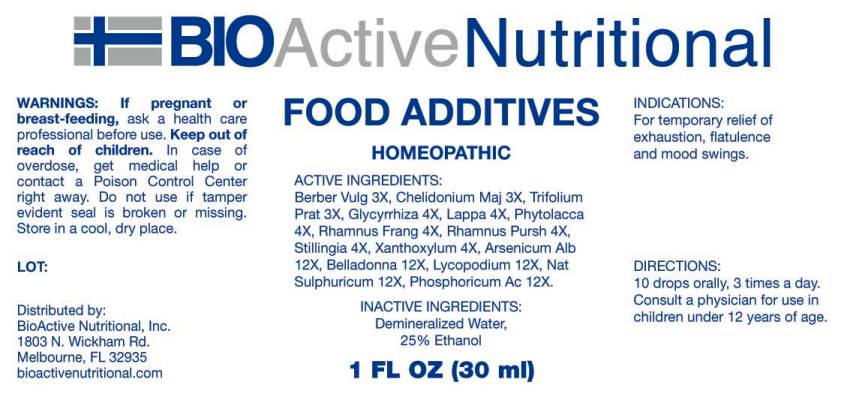 DRUG LABEL: Food Additives
NDC: 43857-0168 | Form: LIQUID
Manufacturer: BioActive Nutritional, Inc.
Category: homeopathic | Type: HUMAN OTC DRUG LABEL
Date: 20160928

ACTIVE INGREDIENTS: BERBERIS VULGARIS ROOT BARK 3 [hp_X]/1 mL; CHELIDONIUM MAJUS 3 [hp_X]/1 mL; TRIFOLIUM PRATENSE FLOWER 3 [hp_X]/1 mL; GLYCYRRHIZA GLABRA 4 [hp_X]/1 mL; ARCTIUM LAPPA ROOT 4 [hp_X]/1 mL; PHYTOLACCA AMERICANA ROOT 4 [hp_X]/1 mL; FRANGULA ALNUS BARK 4 [hp_X]/1 mL; FRANGULA PURSHIANA BARK 4 [hp_X]/1 mL; STILLINGIA SYLVATICA ROOT 4 [hp_X]/1 mL; ZANTHOXYLUM AMERICANUM BARK 4 [hp_X]/1 mL; ARSENIC TRIOXIDE 12 [hp_X]/1 mL; ATROPA BELLADONNA WHOLE 12 [hp_X]/1 mL; LYCOPODIUM CLAVATUM SPORE 12 [hp_X]/1 mL; SODIUM SULFATE 12 [hp_X]/1 mL; PHOSPHORIC ACID 12 [hp_X]/1 mL
INACTIVE INGREDIENTS: WATER; ALCOHOL

Drug Facts:

ACTIVE INGREDIENTS:

Berberis Vulgaris 3X, Chelidonium Majus 3X, Trifolium Pratense 3X, Glycyrrhiza Glabra 4X, Lappa Major 4X, Phytolacca Decandra 4X, Rhamnus Frangula 4X, Rhamnus Purshiana 4X, Stillingia Sylvatica 4X, Xanthoxylum Fraxineum 4X, Arsenicum Album 12X, Belladonna 12X, Lycopodium Clavatum 12X, Natrum Sulphuricum 12X, Phosphoricum Acidum 12X

INDICATIONS:

For temporary relief of exhaustion, flatulence and mood swings.

WARNINGS:

If pregnant or breast-feeding, ask a health care professional before use.

Keep out of reach of children. In case of overdose, get medical help or contact a Poison Control Center right away.

Do not use if tamper evident seal is broken or missing.

DIRECTIONS:

10 drops orally, 3 times a day. Consult a physician for use in children under 12 years of age.

INACTIVE INGREDIENTS:

Demineralized Water, 25% Ethanol.

Keep out of reach of children. In case of overdose, get medical help or contact a Poison Control Center right away.

INDICATIONS:

For temporary relief of exhaustion, flatulence and mood swings.

QUESTIONS:

Distributed by:
BioActive Nutritional, Inc.
1803 N. Wickham Rd.
Melbourne, FL 32935
bioactivenutritional.com

PACKAGE LABEL DISPLAY:

BIOActive Nutritional

FOOD ADDITIVES

HOMEOPATHIC

1 FL OZ (30 ml)